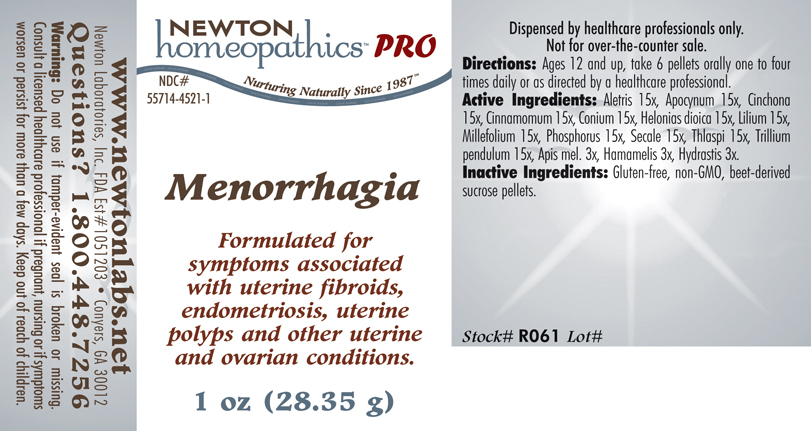 DRUG LABEL: Menorrhagia 
NDC: 55714-4521 | Form: PELLET
Manufacturer: Newton Laboratories, Inc.
Category: homeopathic | Type: HUMAN PRESCRIPTION DRUG LABEL
Date: 20110601

ACTIVE INGREDIENTS: Aletris Farinosa Root 15 [hp_X]/1 g; Apocynum Cannabinum Root 15 [hp_X]/1 g; Cinchona Officinalis Bark 15 [hp_X]/1 g; Cinnamon 15 [hp_X]/1 g; Conium Maculatum Flowering Top 15 [hp_X]/1 g; Chamaelirium Luteum Root 15 [hp_X]/1 g; Lilium Lancifolium Whole Flowering 15 [hp_X]/1 g; Achillea Millefolium 15 [hp_X]/1 g; Phosphorus 15 [hp_X]/1 g; Claviceps Purpurea Sclerotium 15 [hp_X]/1 g; Capsella Bursa-pastoris 15 [hp_X]/1 g; Trillium Erectum Root 15 [hp_X]/1 g; Apis Mellifera 3 [hp_X]/1 g; Hamamelis Virginiana Root Bark/stem Bark 3 [hp_X]/1 g; Goldenseal 3 [hp_X]/1 g
INACTIVE INGREDIENTS: Sucrose

Menorrhagia

INDICATIONS & USAGE SECTION

Menorrhagia Formulated for associated symptoms such as uterine fibroids, uterine polyps, endometriosis and other uterine and ovarian conditions.

DOSAGE & ADMINISTRATION SECTION

Directions: Ages 12 and up, take 6 pellets orally one to four times daily or as directed by a healthcare professional.

ACTIVE INGREDIENT SECTION

Aletris 15x, Apocynum 15x, Cinchona 15x, Cinnamomum 15x, Conium 15x, Helonias dioica 15x, Lilium 15x, Millefolium 15x, Phosphorus 15x, Secale 15x, Thlaspi 15x, Trillium pendulum 15x, Apis mel. 3x, Hamamelis 3x, Hydrastis 3x.

PURPOSE SECTION

Formulated for associated symptoms such as uterine fibroids, uterine polyps, endometriosis and other uterine and ovarian conditions.

INACTIVE INGREDIENT SECTION

Inactive Ingredients: Gluten-free, non-GMO, beet-derived sucrose pellets.

QUESTIONS SECTION

www.newtonlabs.net Newton Laboratories, Inc. FDA Est # 1051203 - Conyers, GA 30012
Questions? 1.800.448.7256

WARNINGS SECTION

Warning: Do not use if tamper - evident seal is broken or missing. Consult a licensed healthcare professional if pregnant, nursing or if symptoms worsen or persist for more than a few days. Keep out of reach of children.

PREGNANCY OR BREAST FEEDING SECTION

Consult a licensed healthcare professional if pregnant, nursing or if symptoms worsen or persist for more than a few days.

KEEP OUT OF REACH OF CHILDREN SECTION

Keep out of reach of children.